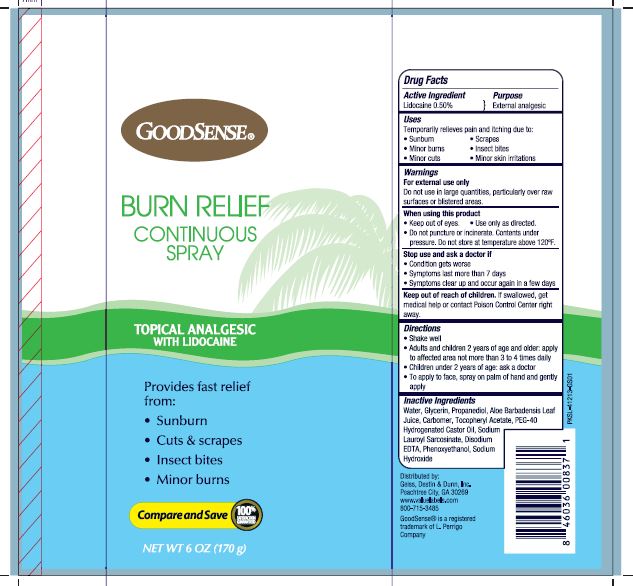 DRUG LABEL: Burn Relief
NDC: 70281-640 | Form: SPRAY
Manufacturer: Solskyn Personal Care LLC
Category: otc | Type: HUMAN OTC DRUG LABEL
Date: 20190716

ACTIVE INGREDIENTS: LIDOCAINE 0.5 g/100 g
INACTIVE INGREDIENTS: .ALPHA.-TOCOPHEROL ACETATE; POLYOXYL 40 HYDROGENATED CASTOR OIL; SODIUM LAUROYL SARCOSINATE; CARBOXYPOLYMETHYLENE; SODIUM HYDROXIDE; WATER; EDETATE DISODIUM; GLYCERIN; PROPANEDIOL; ALOE VERA LEAF; PHENOXYETHANOL

GoodSense Burn Relief Spray 6oz

Active Ingredient

Lidocaine 0.5%

Purpose

External analgesic

Use

INDICATIONS & USAGE SECTION

Temporarily relieves pain and itching due to:
• Sunburn • Minor burns
• Minor cuts • Scrapes
• Insect bites • Minor skin irritations

Dosage & Administration

For the temporary relief of itching associated with minor skin irritations and rashes due to eczema, insect bites, and poison oak.

Warnings

For external use only.

Do not use in large quantities, particularly over raw surfaces or
blistered areas.

When using this product:

• Keep out of eyes.
• Use only as directed.
• Do not puncture or incinerate. Contents under pressure. Do
not store at temperature above 120°F.

Stop use and ask a doctor if:

• Condition gets worse
• Symptoms last more than 7 days
• Symptoms clear up and occur again in a few days

Keep out of reach of children. If swallowed, get medical help or
contact Poison Control Center right away.

Directions

• Shake well
• Adults and children 2 years of age and older: apply to
affected area not more than 3 to 4 times daily
• Children under 2 years of age: ask a doctor
• To apply to face, spray on palm of hand and gently apply

Inactive Ingredients

Water, Glycerin, Propanediol, Aloe Barbadensis Leaf Juice,
Carbomer, Tocopheryl Acetate, PEG-40 Hydrogenated Castor Oil,
Sodium Lauroyl Sarcosinate, Disodium EDTA, Phenoxyethanol,
Sodium Hydroxide

Questions or comments?

Distributed by:

Geiss, Destin & Dunn, Inc.

Peachtree City, GA 30269

www.valuelabels.com

800-715-3485

Principal Display Panel

GoodSense

Burn Relief

Continuous Spray

Topical Analgesic

With LidocainepROVIDES FAST RELIEF FROM:

- Sunburn
- Cuts & scrapes
- Insect bites,
- Minor burn & sunburn

Compare and Save 100% Satisfaction Guaranteed

NET WT 6 OZ (170 g)